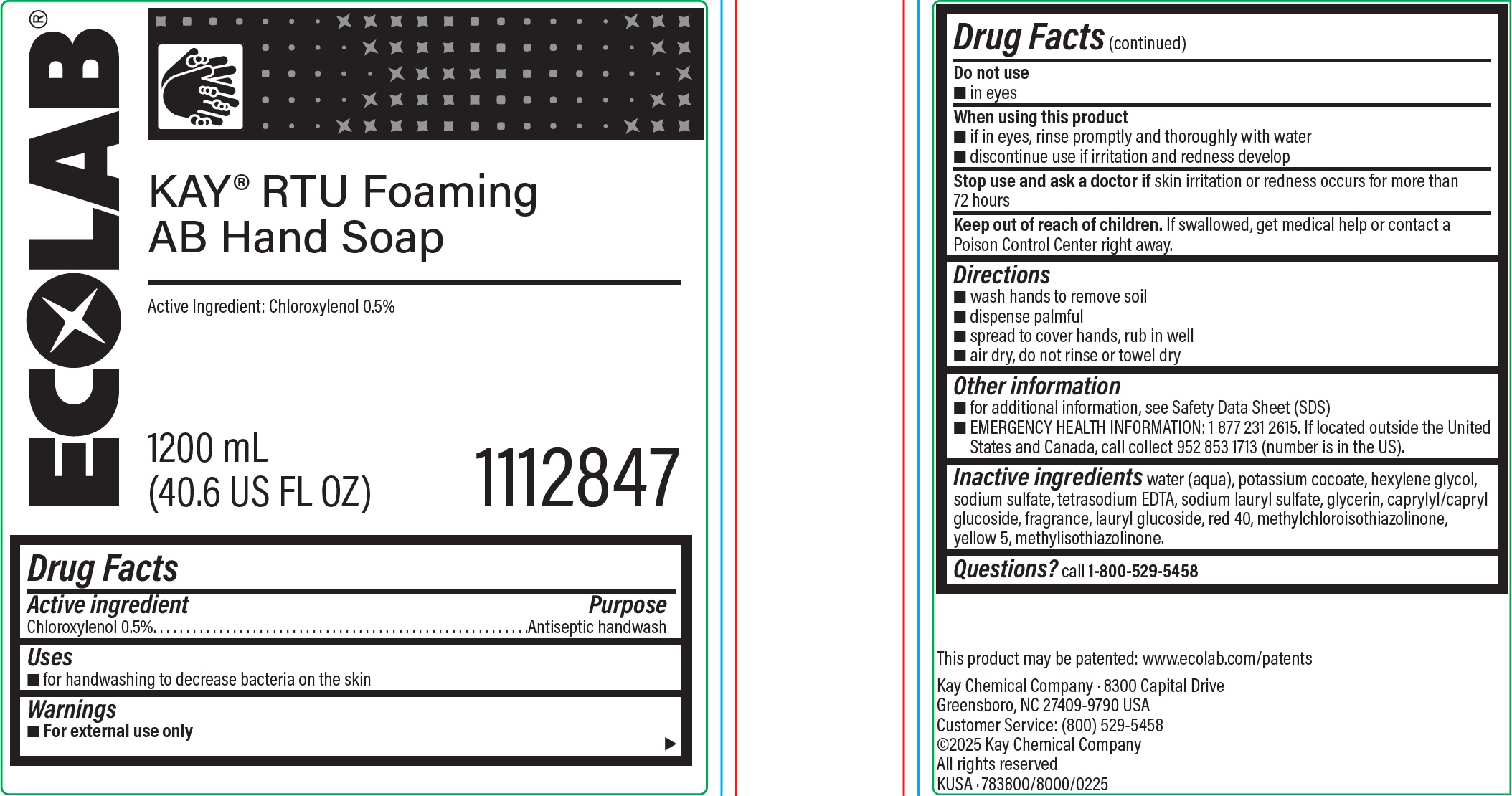 DRUG LABEL: Kay RTU Foaming AB HandSoap
NDC: 47593-693 | Form: SOLUTION
Manufacturer: Ecolab Inc.
Category: otc | Type: HUMAN OTC DRUG LABEL
Date: 20251230

ACTIVE INGREDIENTS: CHLOROXYLENOL 5 mg/1 mL
INACTIVE INGREDIENTS: WATER; POTASSIUM COCOATE; HEXYLENE GLYCOL; SODIUM SULFATE; EDETATE SODIUM; SODIUM LAURYL SULFATE; GLYCERIN; CAPRYLYL/CAPRYL GLUCOSIDE; LAURYL GLUCOSIDE; FD&C RED NO. 40; METHYLCHLOROISOTHIAZOLINONE; FD&C YELLOW NO. 5; METHYLISOTHIAZOLINONE

Drug Facts

Active ingredient

Chloroxylenol 0.5%

Purpose

Antiseptic Handwash

Uses

- for handwashing to decrease bacteria on the skin.

Warnings

- For external use only

Do not use

- In eyes

When using this product

- If in eyes, rinse promptly and thoroughly with water
- Discontinue use if irritation and redness develop

Stop use and ask a doctor if

- Skin irritation or redness occurs for more than 72 hours

Keep out of reach of children.

If swallowed, get medical help or contact a Poison Control Center right away.

Directions

- Wet hands to remove soil
- Dispense palmful
- spread to cover hands, rub in well
- air dry, do not rinse or towel dry

Other Information

- for additional information, see Safety Data Sheet (SDS)
- EMERGENCY HEALTH INFORMATION: 1 877 231 2615. If located outside the United States and Canada, call collect 952 853 1713 (number is in the US).

INACTIVE INGREDIENT

Inactive ingredients water (aqua), potassium cocoate, hexylene glycol, sodium sulfate, tetrasodium EDTA, sodium lauryl sulfate, glycerin, caprylyl/capryl glucoside, fragrance, lauryl glucoside, red 40, methylchloroisothiazolinone, yellow 5, methylisothiazolinone

Questions? Call 1-800-529-5458

Principal display panel and representative label

ECOLAB

Kay RTU Foaming AB Hand Soap

Active Ingredient: Chloroxylenol 0.5%

1200 mL

(40.6 US FL OZ)

1112847

Kay Chemical Company · 8300 Capital Drive

Greensboro, NC 27409-9790 USA

Customer Service: (800) 529-5458

©2025 Kay Chemical Company

All rights reserved

KUSA · 783800/8000/0225